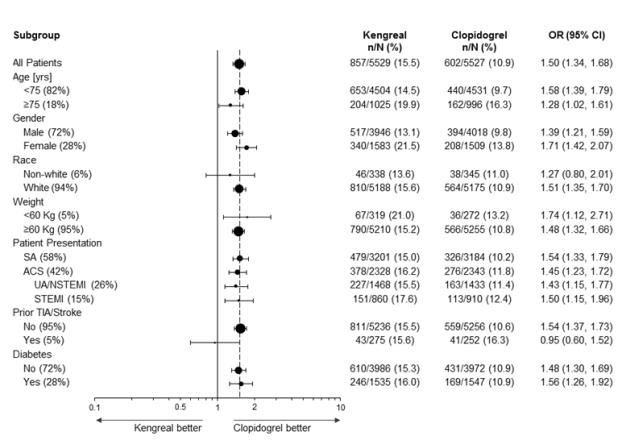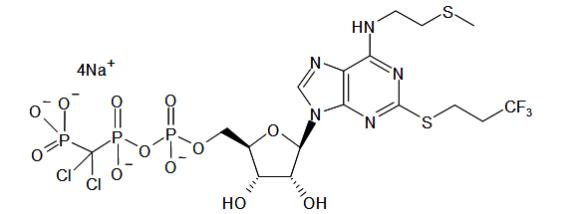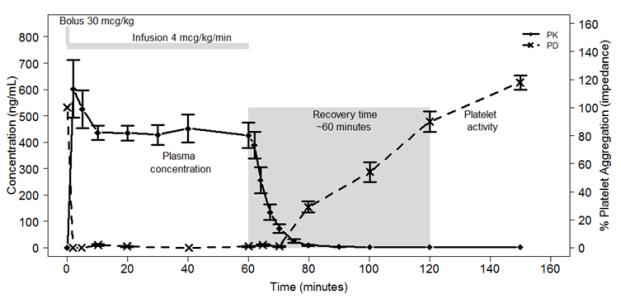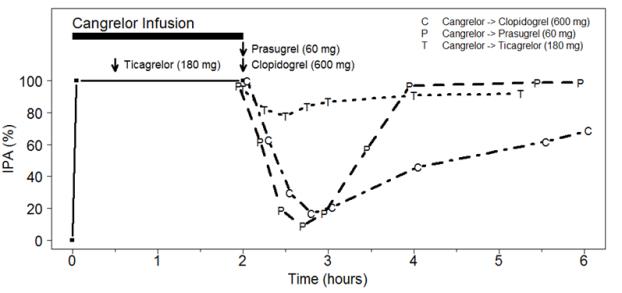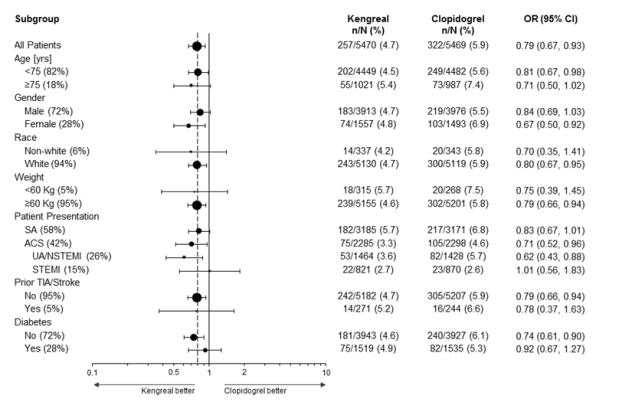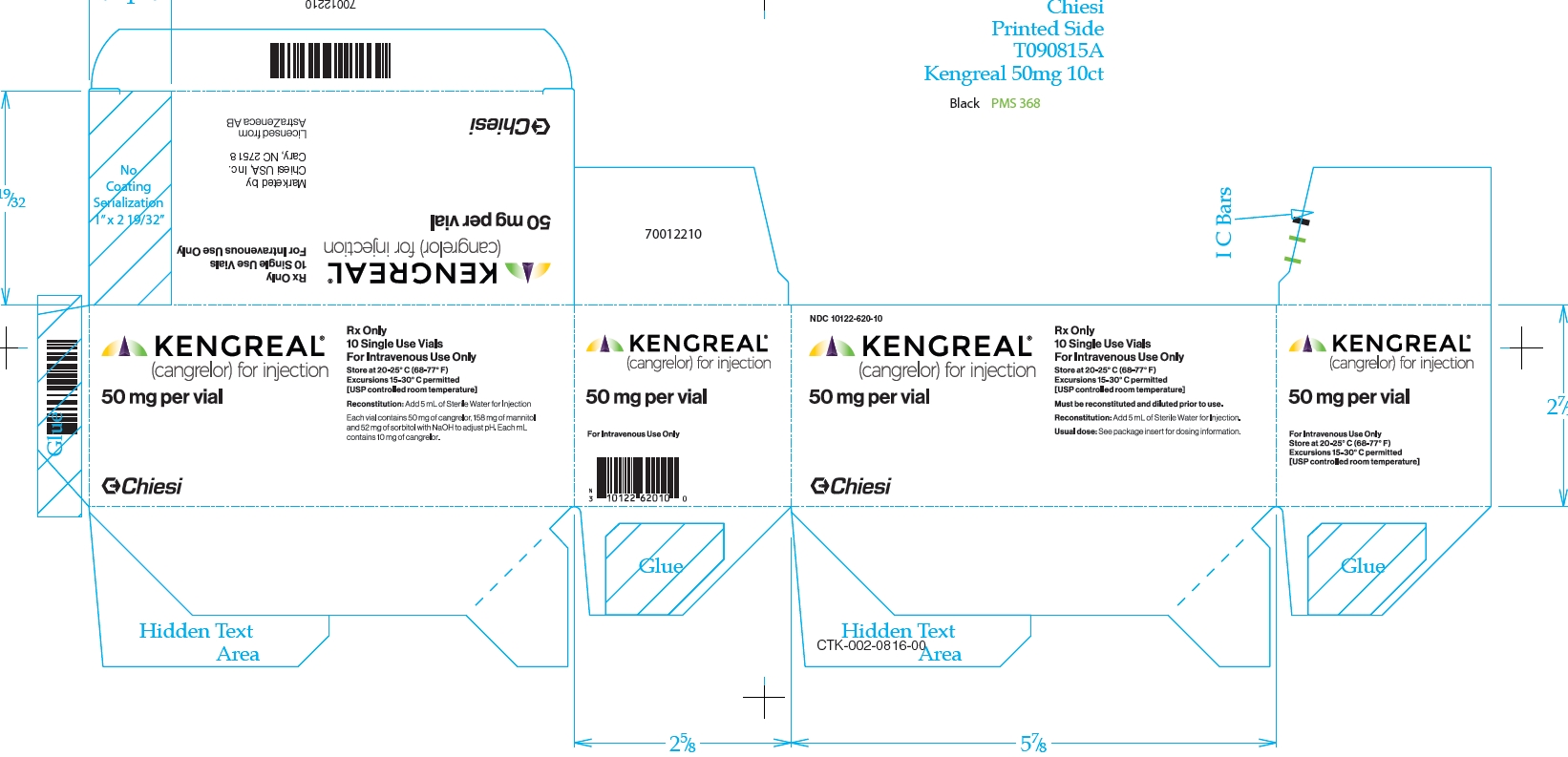 DRUG LABEL: KENGREAL
NDC: 10122-620 | Form: INJECTION, POWDER, LYOPHILIZED, FOR SOLUTION
Manufacturer: Chiesi USA, Inc.
Category: prescription | Type: HUMAN PRESCRIPTION DRUG LABEL
Date: 20251021

ACTIVE INGREDIENTS: CANGRELOR 50 mg/1 1
INACTIVE INGREDIENTS: MANNITOL 158 mg/1 1; SORBITOL 52 mg/1 1; SODIUM HYDROXIDE

HIGHLIGHTS OF PRESCRIBING INFORMATION

These highlights do not include all the information needed to use KENGREAL safely and effectively. See full prescribing information for KENGREAL.
KENGREAL® (cangrelor) for injection, for intravenous use
Initial U.S. Approval: 2015

1 INDICATIONS AND USAGE

KENGREAL is a P2Y12 platelet inhibitor indicated as an adjunct to percutaneous coronary intervention (PCI) for reducing the risk of periprocedural myocardial infarction (MI), repeat coronary revascularization, and stent thrombosis (ST) in patients in who have not been treated with a P2Y12 platelet inhibitor and are not being given a glycoprotein IIb/IIIa inhibitor. (1)

2 DOSAGE AND ADMINISTRATION

- KENGREAL is intended for administration via a dedicated IV line, only after reconstitution and dilution. (2.3)
- Administer 30 mcg/kg intravenous (IV) bolus prior to PCI followed immediately by a 4 mcg/kg/min IV infusion for at least 2 hours or duration of procedure, whichever is longer. (2.1)
- To maintain platelet inhibition after discontinuation of KENGREAL infusion, administer an oral P2Y12 platelet inhibitor. (2.2)

3 DOSAGE FORMS AND STRENGTHS

Single-use 10 mL vial containing 50 mg KENGREAL as a lyophilized powder for reconstitution (3.0)

4 CONTRAINDICATIONS

- Significant active bleeding (4.1)
- Hypersensitivity to KENGREAL or any component of the product (4.2)

5 WARNINGS AND PRECAUTIONS

- Bleeding: Like other drugs that inhibit platelet P2Y12 function, KENGREAL can increase the risk of bleeding (5.1)

6 ADVERSE REACTIONS

The most common adverse reaction is bleeding. (5.1, 6.1)

To report SUSPECTED ADVERSE REACTIONS, contact Chiesi USA, Inc. at 1-888-661-9260 or FDA at 1-800-FDA-1088 or www.fda.gov/medwatch.

7 DRUG INTERACTIONS

- Clopidogrel: Do not administer during KENGREAL infusion. (7.1)
- Prasugrel: Do not administer during KENGREAL infusion. (7.1)

FULL PRESCRIBING INFORMATION

1 INDICATIONS AND USAGE

KENGREAL is indicated as an adjunct to percutaneous coronary intervention (PCI) to reduce the risk of periprocedural myocardial infarction (MI), repeat coronary revascularization, and stent thrombosis (ST) in patients who have not been treated with a P2Y12 platelet inhibitor and are not being given a glycoprotein IIb/IIIa inhibitor [see Clinical Studies (14.1)].

2 DOSAGE AND ADMINISTRATION

2.1 Recommended Dosing

The recommended dosage of KENGREAL is a 30 mcg/kg IV bolus followed immediately by a 4 mcg/kg/min IV infusion. Initiate the bolus infusion prior to PCI. The maintenance infusion should ordinarily be continued for at least 2 hours or for the duration of PCI, whichever is longer.

2.2 Transitioning Patients to Oral P2Y 12 Therapy

To maintain platelet inhibition after discontinuation of KENGREAL infusion, administer an oral P2Y12 platelet inhibitor, as described below:

- Ticagrelor: 180 mg at any time during KENGREAL infusion or immediately after discontinuation [see Clinical Pharmacology (12.2)].
- Prasugrel: 60 mg immediately after discontinuation of KENGREAL [see Drug Interactions (7.1) and Clinical Pharmacology (12.2)].
- Clopidogrel: 600 mg immediately after discontinuation of KENGREAL [see Drug Interactions (7.1) and Clinical Pharmacology (12.2)].

2.3 Preparation and Administration

KENGREAL is intended for IV administration, after reconstitution and dilution.

Preparation

Reconstitute the vial prior to dilution in a bag. For each 50 mg/vial, reconstitute by adding 5 mL of Sterile Water for Injection. Swirl gently until all material is dissolved. Avoid vigorous mixing. Allow any foam to settle. Ensure that the contents of the vial are fully dissolved and the reconstituted material is a clear, colorless to pale yellow solution. Parenteral drug products should be inspected visually for particulate matter after reconstitution.

Before administration, each reconstituted vial must be diluted further with Normal Saline (Sodium Chloride Injection 0.9% USP) or 5% Dextrose Injection USP.

Withdraw the contents from one reconstituted vial and add to one 250 mL saline bag. Mix the bag thoroughly. This dilution will result in a concentration of 200 mcg/mL and should be sufficient for at least 2 hours of dosing. Patients 100 kg and over will require a minimum of 2 bags.

Reconstituted KENGREAL should be diluted immediately. Diluted KENGREAL is stable for up to 12 hours in 5% Dextrose Injection and 24 hours in Normal Saline at Room Temperature. Discard any unused portion of reconstituted solution remaining in the vial.

Administration

Administer KENGREAL via a dedicated IV line.

Administer the bolus volume rapidly (<1 minute), from the diluted bag via manual IV push or pump. Ensure the bolus is completely administered before the start of PCI. Start the infusion immediately after administration of the bolus [see Dosage and Administration (2.1)].

3 DOSAGE FORMS AND STRENGTHS

For Injection: 50 mg of KENGREAL lyophilized powder in a single-use 10 mL glass vial for reconstitution.

4 CONTRAINDICATIONS

4.1 Significant Active Bleeding

KENGREAL is contraindicated in patients with significant active bleeding [see Warnings and Precautions (5.1) and Adverse Reactions (6.1)].

4.2 Hypersensitivity

KENGREAL is contraindicated in patients with known hypersensitivity (e.g., anaphylaxis) to KENGREAL or any component of the product [see Adverse Reactions (6.1)].

5 WARNINGS AND PRECAUTIONS

5.1 Bleeding

Drugs that inhibit platelet P2Y12 function, including KENGREAL, increase the risk of bleeding.

In CHAMPION PHOENIX bleeding events of all severities were more common with KENGREAL than with clopidogrel [see Adverse Reactions (6.1)]. Bleeding complications with KENGREAL were consistent across a variety of clinically important subgroups (see Figure 1).

Once KENGREAL is discontinued, there is no antiplatelet effect after an hour [see Clinical Pharmacology (12.3)].

6 ADVERSE REACTIONS

The following adverse reactions are also discussed elsewhere in the labeling:

- Bleeding [see Warnings and Precautions (5.1)]

6.1 Clinical Trials Experience

Because clinical trials are conducted under widely varying conditions, adverse reactions rates observed in the clinical trials of a drug cannot be directly compared to rates in the clinical trials of another drug and may not reflect the rates observed in practice.

The safety of KENGREAL has been evaluated in 13,301 subjects in controlled trials, in whom, 5,529 were in the CHAMPION PHOENIX trial.

Bleeding

There was a greater incidence of bleeding with KENGREAL than with clopidogrel. No baseline demographic factor altered the relative risk of bleeding with KENGREAL (see Table 1 and Figure 1).

Table 1: Major Bleeding Results in the CHAMPION PHOENIX Study (Non-CABG related Bleeding)a
CHAMPION PHOENIX | KENGREAL (N=5529) | Clopidogrel (N=5527)
Any GUSTO bleeding, n (%) | 857 (15.5) | 602 (10.9)
Severe/life-threatening b | 11 (0.2) | 6 (0.1)
Moderate c | 21 (0.4) | 14 (0.3)
Mild d | 825 (14.9) | 582 (10.5)
Any TIMI bleeding, n (%) | 45 (0.8) | 17 (0.3)
Major e | 12 (0.2) | 6 (0.1)
Minor f | 33 (0.6) | 11 (0.2)

Abbreviations: GUSTO: Global Utilization of Streptokinase and Tissue Plasminogen Activator for Occluded Arteries; TIMI: Thrombolysis in Myocardial Infarction

a Safety population is all randomized subjects who received at least one dose of study drug

b intracranial hemorrhage or bleeding resulting in substantial hemodynamic compromise requiring treatment

c requiring blood transfusion but not resulting in hemodynamic compromise

d all other bleeding not included in severe or moderate

e any intracranial hemorrhage, or any overt bleeding associated with a reduction in hemoglobin of ≥5 g/dL (or, when hemoglobin is not available, an absolute reduction in hematocrit ≥15%)

f any overt sign of bleeding (including observation by imaging techniques) that is associated with a reduction in hemoglobin of ≥3 g/dL and <5 g/dL (or, when hemoglobin is not available, an absolute reduction in hematocrit of ≥9% and <15%)

Figure 1: Bleeding Results in the CHAMPION PHOENIX Studya (All Non-CABG related)

a Safety population is all randomized subjects who received at least one dose of study drug

Note: The figure above presents effects in various subgroups most of which are baseline characteristics and most of which were pre-specified (patient presentation and weight were not pre-specified subgroups). The 95% confidence limits that are shown do not take into account how many comparisons were made, nor do they reflect the effect of a particular factor after adjustment for all other factors. Apparent homogeneity or heterogeneity among groups should not be over-interpreted.

Drug Discontinuation

In CHAMPION PHOENIX the rate of discontinuation for bleeding events was 0.3% for KENGREAL and 0.1% for clopidogrel. Discontinuation for non-bleeding adverse events was low and similar for KENGREAL (0.6%) and for clopidogrel (0.4%). Coronary artery dissection, coronary artery perforation, and dyspnea were the most frequent events leading to discontinuation in patients treated with KENGREAL.

Non-Bleeding Adverse Reactions

Hypersensitivity

Serious cases of hypersensitivity were more frequent with KENGREAL (7/13301) than with control (2/12861). These included anaphylactic reactions, anaphylactic shock, bronchospasm, angioedema, and stridor.

Decreased renal function

Worsening renal function was reported in 3.2% of KENGREAL patients with severe renal impairment (creatinine clearance <30 mL/min) compared to 1.4% of clopidogrel patients with severe renal impairment.

Dyspnea

Dyspnea was reported more frequently in patients treated with KENGREAL (1.3%) than with control (0.4%).

7 DRUG INTERACTIONS

7.1 Thienopyridines

Clopidogrel or prasugrel administered during KENGREAL infusion will have no antiplatelet effect until the next dose is administered. Therefore, administer clopidogrel or prasugrel after KENGREAL infusion is discontinued [see Dosage and Administration (2.2) and Clinical Pharmacology (12.3)].

8 USE IN SPECIFIC POPULATIONS

8.1 Pregnancy

Risk Summary

There are no available data on cangrelor use in pregnant women to evaluate for a drug-associated risk of major birth defects, miscarriage or adverse maternal or fetal outcomes. Untreated myocardial infarction can be fatal to the pregnant women and fetus (see Clinical Considerations).

In animal reproduction studies, continuous infusion of cangrelor in pregnant rats and rabbits throughout organogenesis at dose approximately 2-times the maximum recommended human dose (MRHD) did not result in fetal malformations (see Data).

The estimated background risk of major birth defects and miscarriage for the indicated population is unknown. All pregnancies have a background risk of birth defect, loss, or other adverse outcomes. In the U.S. general population, the estimated background risk of major birth defects and miscarriage in clinically recognized pregnancies is 2-4% and 15-20%, respectively.

Clinical Considerations

Disease-associated maternal and/or embryo/fetal risk

Myocardial infarction is a medical emergency in pregnancy which can be fatal to the pregnant woman and fetus if left untreated. Life-sustaining therapy for the pregnant woman should not be withheld due to potential concerns regarding the effects of cangrelor on the fetus.

Labor or delivery

Cangrelor use during labor and delivery may increase the risk for maternal bleeding and hemorrhage. Performance of neuraxial blockade procedures is not advised during cangrelor use due to potential risk of spinal hematoma. When possible, discontinue cangrelor 1 hour prior to labor, delivery, or neuraxial blockade [see Clinical Pharmacology (12.2)].

Data

Animal Data

A prenatal and postnatal development study in female rats demonstrated a slight increase in the incidence of maternal mortality in dams treated at doses up to 30 mcg/kg/min (approximately 7.5 times the MRHD) cangrelor continuous infusion from Day 6 of gestation up to Day 23 post-partum. Pregnancy rates, gestation index, length of gestation, numbers of live, dead and malformed pups, sex ratio, live birth index, and lactation of the maternal animals were unaffected.

Cangrelor administered at dose levels of ≥ 3 mcg/kg/min in pregnant rats from Day 6 to 17 post-coitum resulted in dose-related fetal growth retardation characterized by increased incidences of incomplete ossification and unossified hind limb metatarsals.

An embryo-fetal development study in rabbits administered 4, 12, or 36 mcg/kg/min cangrelor continuous IV infusion from Day 6 to Day 19 post-coitum resulted in increased incidences of abortion and intrauterine losses at ≥12 mcg/kg/min (3 times the MRHD). Fetal growth retardation occurred at 36 mcg/kg/min (9 times the MRHD) and was characterized by decreased fetal weights, slight reduction in ossification, and a slight increase in skeletal variants.

Cangrelor did not produce malformations in either the rat or rabbit embryo-fetal development studies and is not considered to be a teratogen.

8.2 Lactation

Risk Summary

There are no data on the presence of cangrelor in human milk or animal milk, the effects on the breastfed infant, or the effects on milk production. However, due to its short-half life, cangrelor exposure is expected to be very low in the breastfed infant.

8.4 Pediatric Use

Safety and effectiveness in pediatric patients have not been established.

8.5 Geriatric Use

In CHAMPION PHOENIX, 18% of patients were ≥75 years. No overall differences in safety or effectiveness were observed between these patients and those patients <75 years [see Clinical Studies (14.1)].

8.6 Renal Impairment

No dosage adjustment is required for patients with mild, moderate, or severe renal impairment [see Clinical Pharmacology (12.3)].

8.7 Hepatic Impairment

KENGREAL has not been studied in patients with hepatic impairment. However, the metabolism of KENGREAL is not dependent of hepatic function, so dosage adjustment is not required for patients with hepatic impairment [see Clinical Pharmacology (12.3)].

10 OVERDOSAGE

There is no specific treatment to reverse the antiplatelet effect of KENGREAL but the effect is gone within one hour after the drug is discontinued.

In clinical trials, 36 patients received an overdose of KENGREAL, ranging from 36 to 300 mcg/kg (bolus dose) or 4.8 to 13.7 mcg/kg/min (infusion dose). The maximum overdose received was 10 times the PCI bolus dose or 3.5 times the PCI infusion dose in 4 patients. No clinical sequela were noted as a result of overdose following completion of KENGREAL therapy.

11 DESCRIPTION

KENGREAL is a direct-acting P2Y12 platelet receptor inhibitor that blocks adenosine diphosphate (ADP)-induced platelet activation and aggregation. The chemical structure is similar to adenosine triphosphate (ATP).

The chemical name of KENGREAL is tetrasodium salt of N6-[2-(methylthio)ethyl]-2-[(3,3,3,-trifluoropropyl)-5’-adenylic acid, monanhydride with (dichloromethylene) bisphosphonic acid.

The empirical formula of KENGREAL is C17H21N5Cl2F3Na4O12P3S2 and the molecular weight is 864.3 g/mol.

The chemical structure is represented below:

Cangrelor for Injection is a sterile white to off-white lyophilized powder for IV infusion. In addition to the active ingredient, cangrelor, each single use vial contains mannitol (158 mg), sorbitol (52 mg), and sodium hydroxide to adjust the pH.

12 CLINICAL PHARMACOLOGY

12.1 Mechanism of Action

Cangrelor is a direct P2Y12 platelet receptor inhibitor that blocks ADP-induced platelet activation and aggregation. Cangrelor binds selectively and reversibly to the P2Y12 receptor to prevent further signaling and platelet activation.

12.2 Pharmacodynamics

Cangrelor inhibits activation and aggregation of platelets. After administration of a 30 mcg/kg IV bolus followed by a 4 mcg/kg/min IV infusion, platelet inhibition occurs within 2 minutes.

Figure 2 shows the effect on platelet activity, and its relation to cangrelor plasma concentration, of administering a 30 mcg/kg IV bolus, followed by a 1-hour 4 mcg/kg/min IV infusion, of cangrelor. The anti-platelet effect is maintained for the duration of the infusion. After discontinuation of the infusion, the anti-platelet effect decreases rapidly and platelet function returns to normal within 1 hour.

Figure 2: Cangrelor PD Characteristics

12.3 Pharmacokinetics

KENGREAL administered intravenously has linear pharmacokinetics in both healthy volunteers and patients. KENGREAL is rapidly distributed and metabolized, reaching Cmax within 2 minutes after administration of an intravenous bolus followed by infusion.

Distribution

In a study in healthy volunteers, KENGREAL administration at a dose of 30 mcg/kg bolus plus 4 mcg/kg/min showed a volume of distribution of 3.9 L. Plasma protein binding of KENGREAL is about 97-98%.

Metabolism

KENGREAL is deactivated rapidly in the circulation by dephosphorylation to its primary metabolite, a nucleoside, which has negligible anti-platelet activity. KENGREAL’s metabolism is independent of hepatic function and it does not interfere with other drugs metabolized by hepatic enzymes.

Elimination

Following IV administration of [^3H] KENGREAL 58% of radioactivity was recovered in urine. The remaining 35% of radioactivity was in feces, presumably following biliary excretion. The average elimination half-life of KENGREAL is about 3-6 minutes.

Specific Populations

KENGREAL pharmacokinetics are not affected by sex, age, renal status or hepatic function. No dose adjustment is needed for these factors [see Use in Specific Populations (8)].

Weight

Although weight was a significant covariate for PK with higher clearance in heavier patients, the impact of weight on drug exposure is accounted by the use of weight-based dosing.

Drug-Drug Interactions

Co-administration of cangrelor with unfractionated heparin, aspirin, and nitroglycerin was formally studied in healthy subjects, with no evidence of an effect on the PK/PD of cangrelor.

In clinical trials cangrelor has been co-administered with bivalirudin, low molecular weight heparin, clopidogrel, prasugrel, and ticagrelor without clinically detectable interactions.

The expected antiplatelet effect of a 600 mg loading dose of clopidogrel or a 60 mg loading dose of prasugrel was blocked when clopidogrel or prasugrel was administered during a cangrelor infusion [see Drug Interactions (7.1)].

In contrast, the antiplatelet effect of a 180 mg ticagrelor loading dose was not altered significantly when ticagrelor was administered during cangrelor infusion [see Drug Interactions (7.1)].

Figure 3: Inhibition (Mean) of 20 µM ADP-induced Platelet Aggregation (IPA) Measured by Light Transmission Aggregometry after Cangrelor 30 mcg/kg Bolus and 120-minute 4 mcg/kg Infusion with Transition to Other Oral P2Y 12 Platelet Inhibitors.

As shown in Figure 3, discontinuation of cangrelor infusion, followed by administration of the irreversible P2Y12 platelet inhibitors clopidogrel or prasugrel led to a 1-hour decrease in IPA followed by an increase in inhibition of platelet aggregation beginning at about one hour. This time course of platelet inhibition reflects the pharmacokinetics of cangrelor (offset) followed by the absorption and metabolism of clopidogrel and prasugrel to active metabolites (onset). Administration of ticagrelor, a reversible P2Y12 platelet inhibitor, during the cangrelor infusion led to minimal decrease in platelet inhibition for approximately 0.5 hour following discontinuation of the cangrelor infusion. Administering ticagrelor during cangrelor infusion does not attenuate the anti-platelet effect of ticagrelor.

In vitro studies suggest that neither cangrelor nor its major metabolites inhibit the activity of the hepatic CYP isoenzymes at therapeutic concentrations. Therefore, cangrelor administration is not expected to interfere with the hepatic metabolism of other concomitantly administered therapeutic agents.

13 NONCLINICAL TOXICOLOGY

13.1 Carcinogenesis, Mutagenesis, Impairment of Fertility

Carcinogenesis

No carcinogenicity studies were conducted.

Mutagenesis

Cangrelor was non-mutagenic and non-clastogenic in genetic toxicology studies, including in vitro bacterial gene mutation assay, mouse lymphoma thymidine kinase assay, chromosome aberration assay in human peripheral lymphocytes, and in vivo bone marrow micronucleus assay in mice.

Impairment of Fertility

Cangrelor had no significant effect on male or female rats fertility treated by continuous infusion for 28 days, or on early embryonic development at steady state plasma concentration (Css) of approximately the same as that achieved in the PCI setting at the MRHD.

14 CLINICAL STUDIES

14.1 CHAMPION PHOENIX Trial

The CHAMPION PHOENIX trial was intended to test whether faster platelet inhibition with cangrelor at the time of PCI would reduce the rate of periprocedural thrombotic events compared to a drug with a slower antiplatelet effect, clopidogrel, given at about the time of PCI. It was a randomized, double-blind study in which patients with coronary artery disease (stable angina, UA/NSTEMI, STEMI) requiring PCI and receiving standard therapy including aspirin and heparin or bivalirudin were randomized 1:1 to KENGREAL (n=5472) or to clopidogrel 300 or 600 mg (n=5470). Patients who had already taken an oral P2Y12 platelet inhibitor were not eligible to enroll. Patients administered glycoprotein IIb/IIIa inhibitors (GPI) or for whom GPI use was planned were also not eligible to enroll. PHOENIX was thus a study of people undergoing PCI who had not been previously treated with anti-platelet therapy other than aspirin.

The primary outcome measure was the first occurrence of any one of the composite endpoint of all-cause mortality, myocardial infarction (MI), ischemia-driven revascularization (IDR), and stent thrombosis (ST) within 48 hours after randomization.

KENGREAL was administered as 30 mcg/kg bolus followed by 4 mcg/kg/min infusion for 2 to 4 hours. Clopidogrel 600 mg was administered immediately at the end of the KENGREAL infusion in patients randomized to KENGREAL. Clopidogrel 300 mg or 600 mg was administered shortly before PCI or shortly afterward, in patients randomized to clopidogrel.

KENGREAL significantly reduced the occurrence of primary composite endpoint events compared to clopidogrel (relative risk reduction [RRR] 22%). Most of the effect was a reduction in post-procedural MIs detected solely by elevations in CK-MB (type 4a MI). KENGREAL did not reduce the risk of death. Table 2 shows the study results for the primary composite endpoint and the contribution of each component to the primary endpoint.

Table 2: Primary Endpoint and Its Component Events at 48 Hours in CHAMPION PHOENIX (mITT populationa)
 | KENGREAL (N=5470) n (%) | Clopidogrel (N=5469) n (%) | KENGREAL vs. clopidogrel
 |  |  | OR (95% CI) | p-value
Primary Endpoint Death/MI/IDR/ST | 257 (4.7) | 322 (5.9) | 0.78 (0.66,0.93) b | 0.005
Death | 18 (0.3) | 18 (0.3)
MI | 202 (3.7) | 254 (4.6)
IDR | 10 (0.2) | 14 (0.3)
ST | 27 (0.5) | 36 (0.7)

Note: if a subject had more than one event at 48 hours, then worst outcome counted (death >MI >IDR >ST)

aThe mITT population is all randomized subjects who received at least one dose of study drug and underwent the index PCI procedure

b Based on logistic model adjusted for loading dose and baseline patient status for primary endpoint

A supplementary analysis was also performed omitting two subcomponent events of the primary endpoint that were of lesser clinical significance: intraprocedural stent thrombosis (defined as a new or increasing thrombus within or adjacent to a deployed stent occurring during the index PCI procedure), and myocardial infarction with less than a 10-fold increase in CK-MB, or with less than a 5-fold increase in CK-MB in the presence of new Q waves or new left bundle branch block (LBBB). These results are shown in Table 3.

Table 3: Supplementary Endpoint and Its Component Events at 48 Hours in CHAMPION PHOENIX (mITT population)
n (%) | KENGREAL (N=5470) | Clopidogrel (N=5469) | KENGREAL vs. clopidogrel OR (95% CI)
Supplementary Endpoint Death/SCAI-MI/IDR/ARC-ST | 79 (1.4) | 114 (2.1) | 0.69 (0.52,0.92)
Death | 18 (0.3) | 18 (0.3)
SCAI-MIa | 48 (0.9) | 80 (1.5)
IDR | 13 (0.2) | 16 (0.3)
ARC-STb | 0 (0.0) | 0 (0.0)

Note: if a subject had more than one event at 48 hours, then worst outcome counted (death >SCAI-MI >IDR >ARC-ST)

aSCAI MI: CK-MB ≥10X ULN, or CK-MB ≥5X ULN with new Q waves or new LBBB

bARC-ST defined according to the ARC definition [Cutlip et al. 2007]

The effect of KENGREAL appeared to be consistent in a variety of pre-specified and other clinically important subgroups (see Figure 4).

Figure 4: CHAMPION PHOENIX Study: Primary Efficacy Endpoint by Subgroup (mITT Populationa)

a The mITT population is all randomized subjects who received at least one dose of study drug and underwent the index PCI procedure.

Note: The figure above presents effects in various subgroups most of which are baseline characteristics and most of which were pre-specified (patient presentation and weight were not pre-specified subgroups). The 95% confidence limits that are shown do not take into account how many comparisons were made, nor do they reflect the effect of a particular factor after adjustment for all other factors. Apparent homogeneity or heterogeneity among groups should not be over-interpreted.

14.2 CHAMPION PCI and PLATFORM Trials

Two additional concurrent clinical trials of the effect of KENGREAL in patients undergoing percutaneous coronary intervention, CHAMPION PCI and CHAMPION PLATFORM were conducted and terminated early for futility. They were completed prior to the design and conduct of CHAMPION PHOENIX. The comparative characteristics and outcomes of each trial are shown in Table 4.

Table 4: Summary of the CHAMPION Trials
 |  | PCI | PLATFORM | PHOENIX
Subjects Randomized (% of planned enrollment) |  | 8,846 (99%) | 5,346 (84%) | 11,145 (100%)
Primary Endpoint at 48 hours |  | Death, MI, or IDR | Death, MI, or IDR | Death, MI, IDR, or ST
Outcome of primary analysis, OR (95% CI) |  | 1.05 (0.88, 1.24) | 0.87 (0.71, 1.07) | 0.78 (0.66, 0.93)
Clopidogrel dose and time in clopidogrel arm |  | 600 mg immediately before PCI | 600 mg immediately after PCI | 300 or 600 mg shortly before or shortly after PCI
Population enrolled (%) | Stable angina | 15% | 5% | 58%
 | UA/NSTEMI | 74% | 95% | 26%
 | STEMI | 11% | Excluded | 16%

16 HOW SUPPLIED/STORAGE AND HANDLING

KENGREAL is supplied as a sterile lyophilized powder in single-use 10 mL vials.

- NDC # 10122-620-01: 10 mL vial containing 50 mg cangrelor
- NDC # 10122-620-10: 10 count of 10 mL vials containing 50 mg cangrelor

Vials of KENGREAL should be stored at USP Controlled Room Temperature, [20°C to 25°C (68°F to 77°F) with excursions between 15°C and 30°C (59°F and 86°F) permitted].

KENGREAL® is a registered trademeark of Chiesi Farmaceutici S.p.A.

Distributed by:
Chiesi USA, Inc.
Cary, NC 27518

US-126-3-SPL

PACKAGE LABEL

Principal Display Panel
NDC 10122-620-10
Kengreal®
(cangrelor) for injection
50 mg per vial
Rx Only
10 Single Use Vials